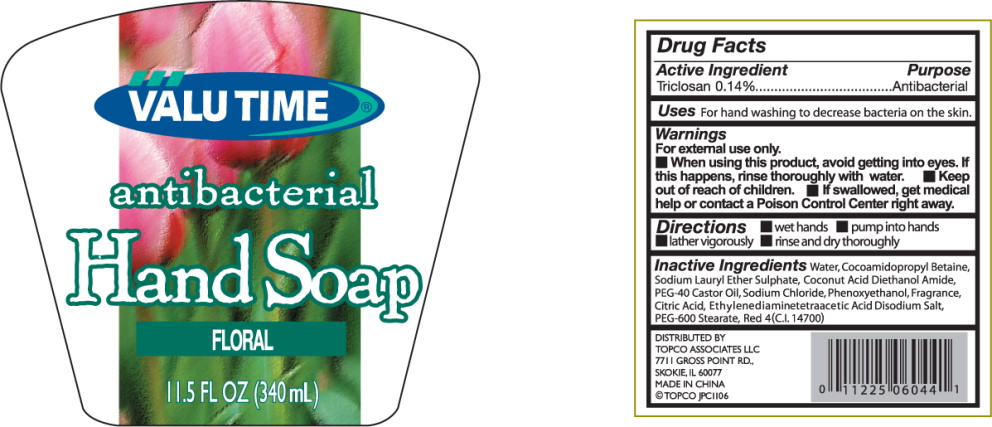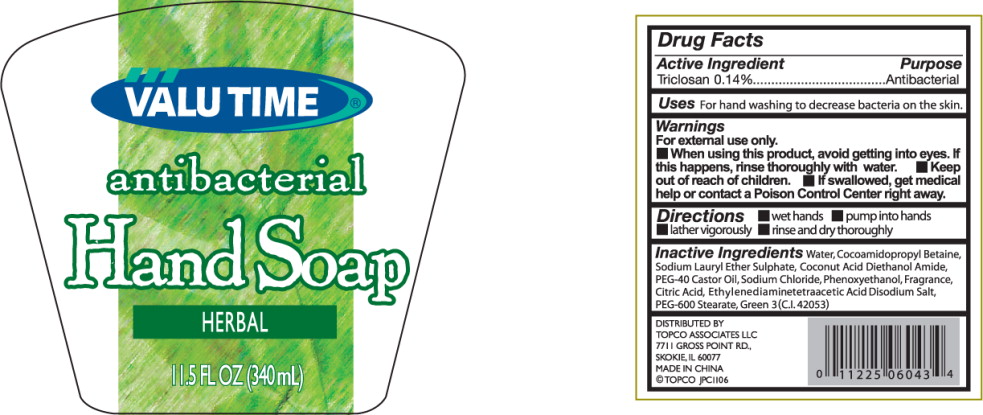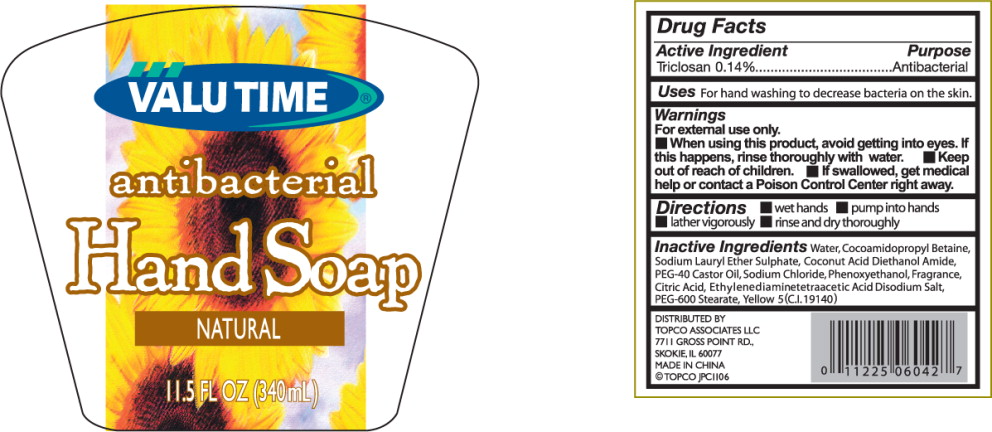 DRUG LABEL: Antibacterial
NDC: 76162-101 | Form: LIQUID
Manufacturer: Topco Associates LLC
Category: otc | Type: HUMAN OTC DRUG LABEL
Date: 20110914

ACTIVE INGREDIENTS: triclosan 0.476 mL/340 mL
INACTIVE INGREDIENTS: water; COCAMIDOPROPYL BETAINE; SODIUM LAURYL SULFATE; COCO DIETHANOLAMIDE; POLYOXYL 40 CASTOR OIL; sodium chloride; phenoxyethanol; CITRIC ACID MONOHYDRATE; EDETATE CALCIUM DISODIUM ANHYDROUS; POLYETHYLENE GLYCOL 600; FD&C RED NO. 4

Drug Facts

Active Ingredient

Triclosan 0.14%

Purpose

Antibacterial

Uses

For hand washing to decrease bacteria on the skin.

Warnings

For external use only.

- When using this product, avoid getting into eyes. If this happens, rinse thoroughly with water.

- Keep out of reach of children.
- If swallowed, get medical help or contact a Poison Control Center right away.

Directions

- wet hands
- pump into hands
- lather vigorously
- rinse and dry thoroughly

Inactive Ingredients

Water, Cocoamidopropyl Betaine, Sodium Lauryl Ether Sulphate, Coconut Acid Diethanol Amide, PEG-40 Castor Oil, Sodium Chloride, Phenoxyethanol, Fragrance, Citric Acid, Ethylenediaminetetraacetic Acid Disodium Salt, PEG-600 Stearate, Red 4(C.I. 14700)

DISTRIBUTED BY
TOPCO ASSOCIATES LLC
7711 GROSS POINT RD.
SKOKIE, IL 60077
MADE IN CHINA
© TOPCO JPC1106

Principal Display Panel – Floral Bottle Label

VALU TIME
antibacterial
Hand Soap
FLORAL
11.5 FL OZ (340mL)

Principal Display Panel – Herbal Bottle Label

VALU TIME
antibacterial
Hand Soap
HERBAL
11.5 FL OZ (340mL)

Principal Display Panel – Natural Bottle Label

VALU TIME
antibacterial
Hand Soap
NATURAL
11.5 FL OZ (340mL)